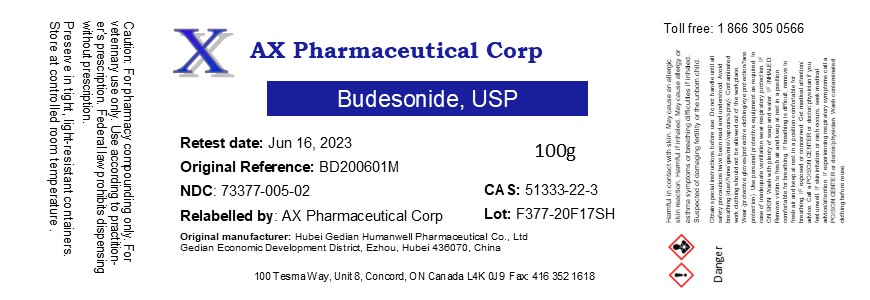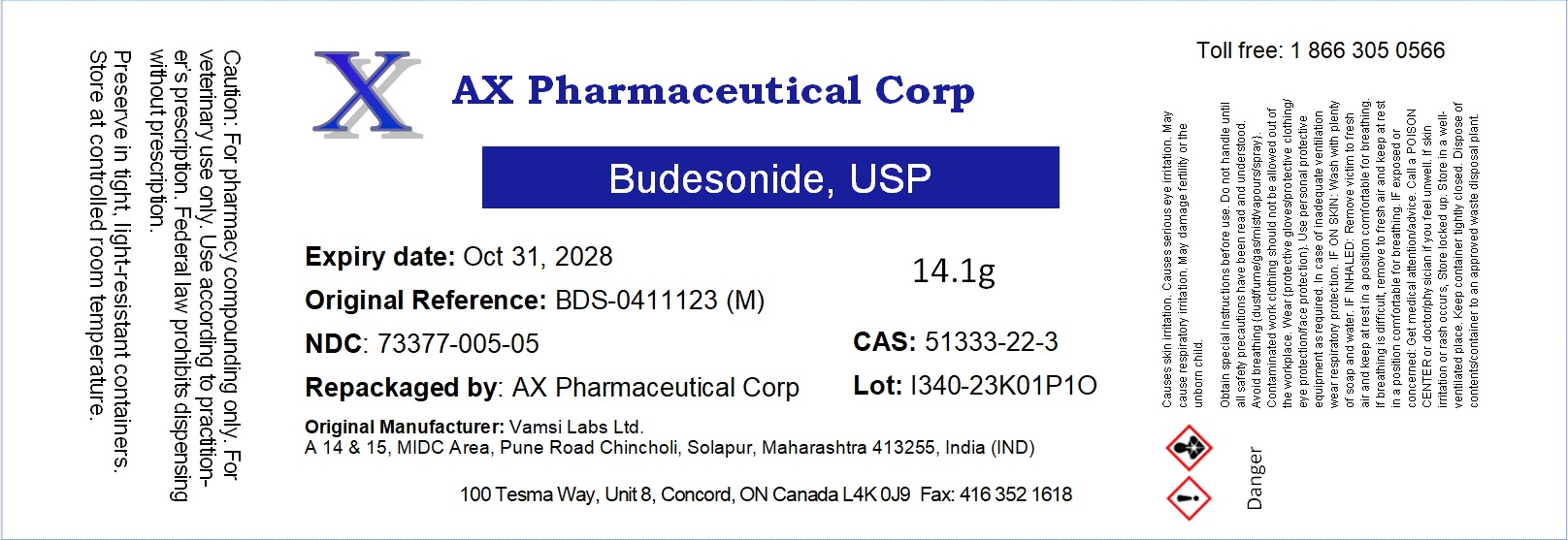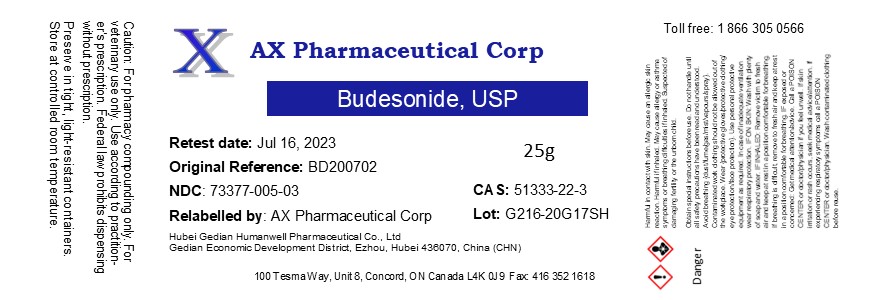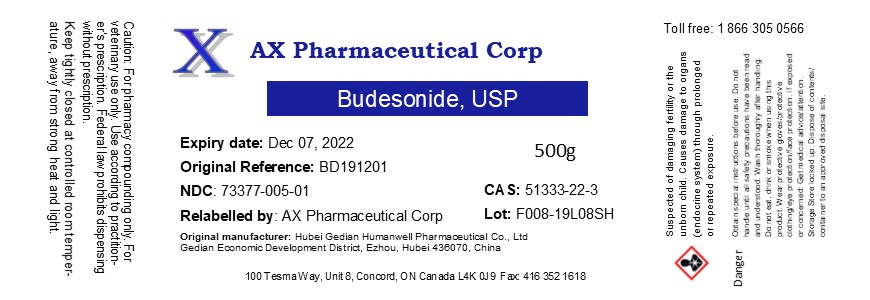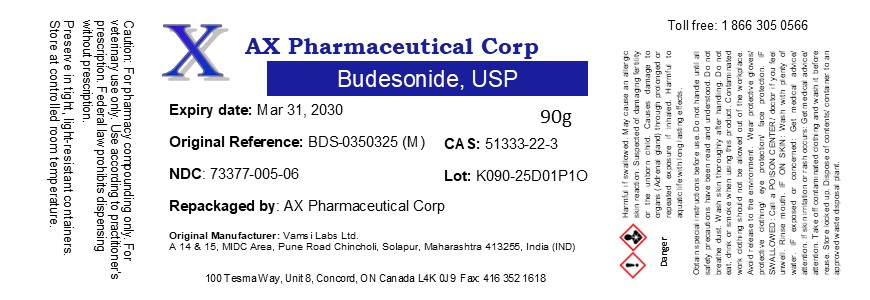 DRUG LABEL: Budesonide
NDC: 73377-005 | Form: POWDER
Manufacturer: AX Pharmaceutical Corp
Category: other | Type: BULK INGREDIENT - ANIMAL DRUG
Date: 20250709

ACTIVE INGREDIENTS: BUDESONIDE 1 g/1 g

Budesonide